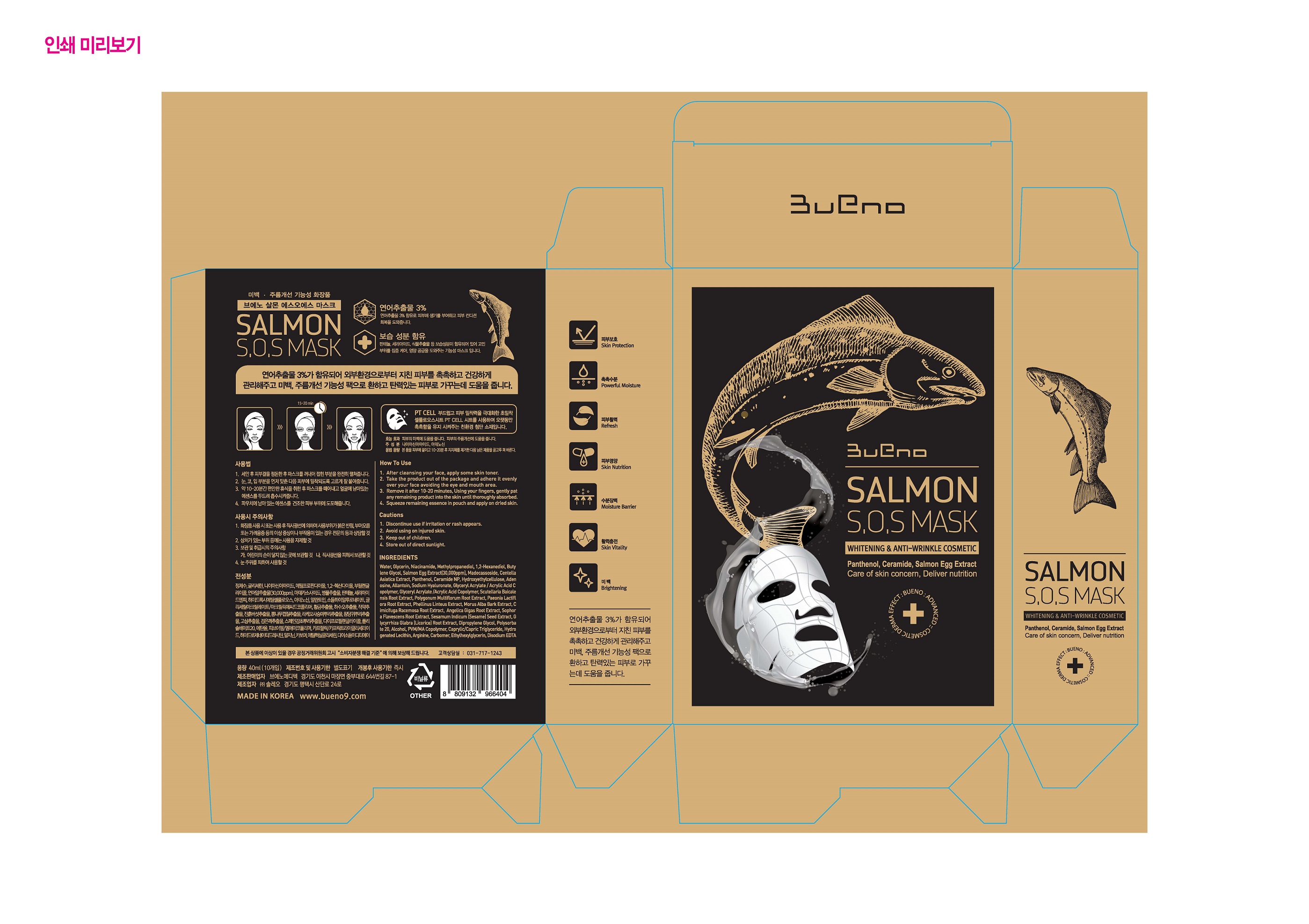 DRUG LABEL: BUENO SALMON S.O.S MASK
NDC: 73261-0001 | Form: PATCH
Manufacturer: Bueno MEDITECH
Category: otc | Type: HUMAN OTC DRUG LABEL
Date: 20190802

ACTIVE INGREDIENTS: GLYCERIN 3.04264 g/100 mL
INACTIVE INGREDIENTS: NIACINAMIDE

Drug Facts

ACTIVE INGREDIENT

glycerin

INACTIVE INGREDIENT

Water
Niacinamide
Methylpropanediol
1,2-Hexanediol
Butylene Glycol
Arginine
Carbomer
Salmon Egg Extract
Hydroxyethylcellulose
Ethylhexylglycerin
Disodium EDTA
Adenosine
Allantoin
Sodium Hyaluronate
Glyceryl Acrylate/Acrylic Acid Copolymer
Dipropylene Glycol
Scutellaria Baicalensis Root Extract
Sophora Flavescens Root Extract
Sesamum Indicum (Sesame) Seed Extract
Polygonum Multiflorum Root Extract
Phellinus Linteus Extract
Panthenol
Paeonia Lactiflora Extract
Morus Alba Bark Extract
Glycyrrhiza Glabra (Licorice) Root Extract
Cimicifuga Racemosa Root Extract
Angelica Gigas Root Extract
PVM/MA Copolymer
Caprylic/Capric Triglyceride
Alcohol
Hydrogenated Lecithin
Centella Asiatica Extract
Ceramide NP
Polysorbate 20
Madecassoside

PURPOSE

whitening & anti-wrinkle

keep out of reach of the children

INDICATIONS AND USAGE

after cleansing your face, apply some skin toner

take the product out of the package and adhere it evenly over your face avoiding the eye and mouth area

remove it after 10-20 minutes, using your fingers, gently pat any remaining product into the skin until thoroughly absorbed

sqeeze remaining essence in pouch and apply on dried skin

WARNINGS

discontinue use if irritation or rash appears

avoid using on injured skin

keep out of childres

store out of direct sunlight

DOSAGE AND ADMINISTRATION

for topical use only